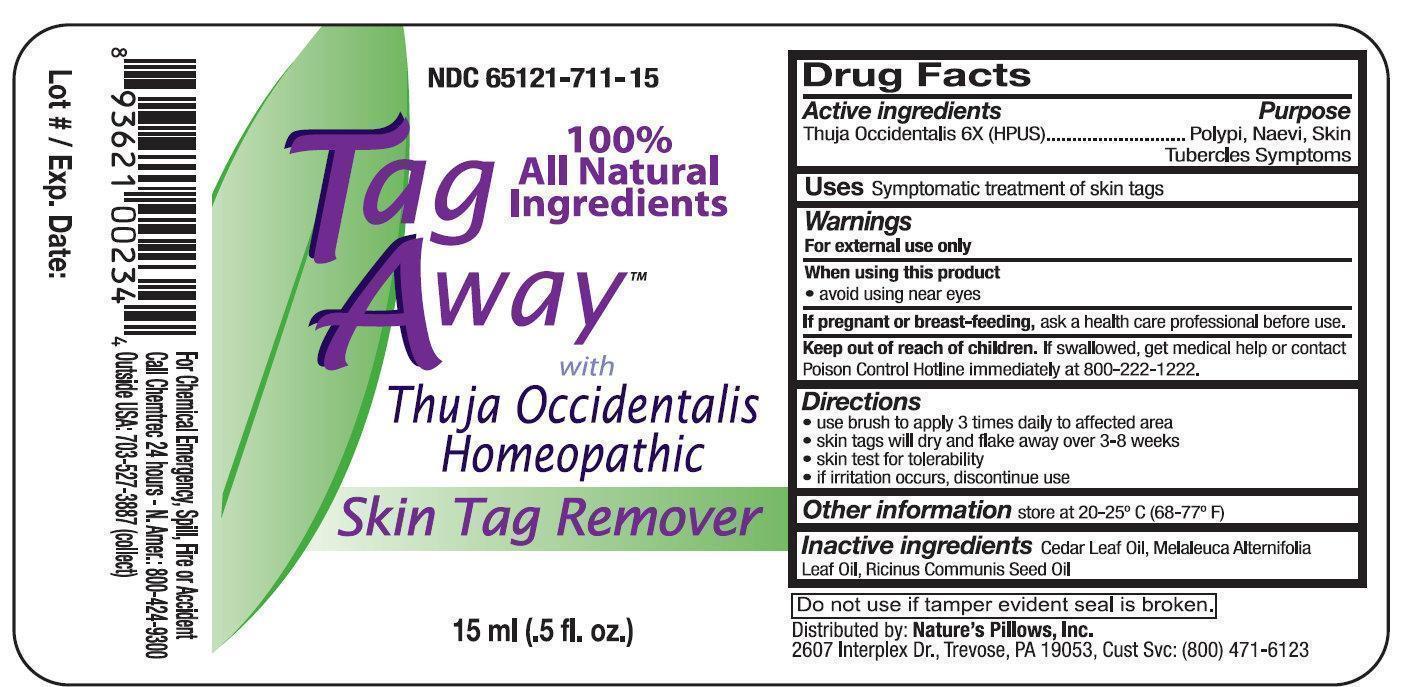 DRUG LABEL: Tag Away
NDC: 65121-711 | Form: LIQUID
Manufacturer: Pure Source, LLC
Category: homeopathic | Type: HUMAN OTC DRUG LABEL
Date: 20170210

ACTIVE INGREDIENTS: THUJA OCCIDENTALIS LEAFY TWIG 6 [hp_X]/1 mL
INACTIVE INGREDIENTS: CEDAR LEAF OIL; TEA TREE OIL; CASTOR OIL

Tag Away

Active Ingredients

Thuja Occidentalis 6X (HPUS)

Uses

Symptomatic treatment of skin tags

Warnings

For external use only

When using this product

- avoid using near eyes

If pregnant or breast-feeding,

ask a health care professional before use.

Directions

- use brush to apply 3 times daily to affected area
- skin tags will dry and flake away over 3-8 weeks
- skin test for tolerability
- if irritation occurs, discontinue use

Other Information

store at 20-25 degrees C (68-77 degrees F)

Inactive Ingredients

Cedar Leaf Oil, Melaleuca Alternifolia Leaf Oil, Ricinus Communis Seed Oil.

Do not use if tamper evident seal is broken.

For Chemical Emergency, Spill, Fire or Accident

Call Chemtrec 24 hours- N. Amer.: 800-424-9300

Outside USA: 703-527-3887 (collect)